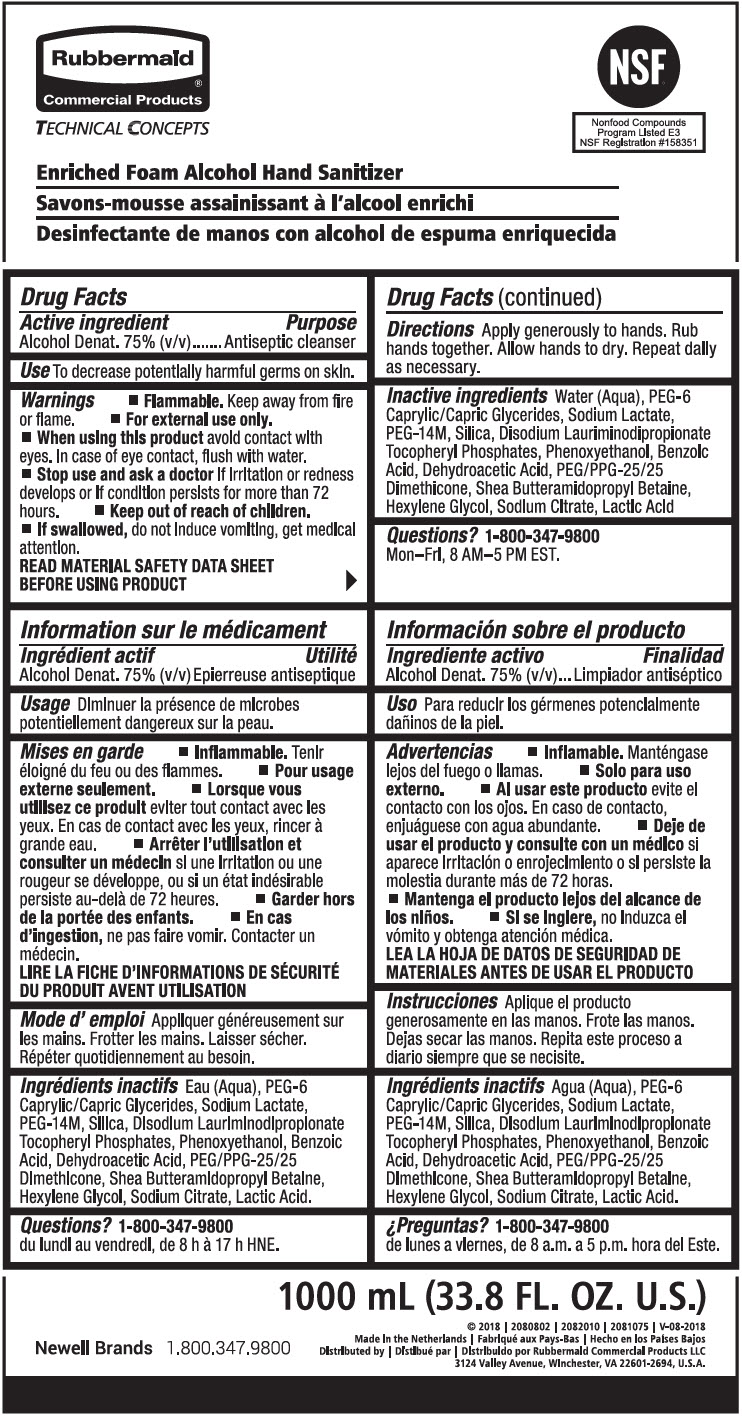 DRUG LABEL: TC Enriched Foam Alcohol Hand Sanitizer
NDC: 65321-036 | Form: LIQUID
Manufacturer: Rubbermaid Commercial Products LLC
Category: otc | Type: HUMAN OTC DRUG LABEL
Date: 20231218

ACTIVE INGREDIENTS: ALCOHOL 70 mg/100 mL
INACTIVE INGREDIENTS: WATER; CAPRYLOCAPROYL POLYOXYLGLYCERIDES 6; SODIUM LACTATE; POLYETHYLENE OXIDE 600000; SILICON DIOXIDE; DISODIUM LAURIMINODIPROPIONATE TOCOPHERYL PHOSPHATES; PHENOXYETHANOL; BENZOIC ACID; DEHYDROACETIC ACID; PEG/PPG-25/25 DIMETHICONE; HEXYLENE GLYCOL; SODIUM CITRATE, UNSPECIFIED FORM; LACTIC ACID, UNSPECIFIED FORM

TC Enriched Foam Alcohol Hand Sanitizer

Drug Facts

Active ingredient

Alcohol Denat. 75% (v/v)

Purpose

Antiseptic cleanser

Use

To decrease potentially harmful germs on skin.

Warnings

- Flammable. Keep away from fire or flame.

- For external use only.

- When using this product avoid contact with eyes. In case of eye contact, flush with water.

- Stop use and ask a doctor if irritation or redness develops or if condition persists for more than 72 hours.

- Keep out of reach of children.

- If swallowed, do not induce vomiting, get medical attention.

READ MATERIAL SAFETY DATA SHEET BEFORE USING PRODUCT

Directions

Apply generously to hands. Rub hands together. Allow hands to dry. Repeat daily as necessary.

Inactive ingredients

Water (Aqua), PEG-6 Caprylic/Capric Glycerides, Sodium Lactate, PEG-14M, Silica, Disodium Lauriminodipropionate Tocopheryl Phosphates, Phenoxyethanol, Benzoic Acid, Dehydroacetic Acid, PEG/PPG-25/25 Dimethicone, Shea Butteramidopropyl Betaine, Hexylene Glycol, Sodium Citrate, Lactic Acid

Questions?

1-800-347-9800

Mon–Fri, 8 AM–5 PM EST.

Distributed by Rubbermaid Commercial Products LLC
3124 Valley Avenue, Winchester, VA 22601-2694, U.S.A.

PRINCIPAL DISPLAY PANEL - 1000 mL Pouch Label

Rubbermaid®
Commercial Products

TECHNICAL CONCEPTS

NSF®

Nonfood Compounds
Program Listed E3
NSF Registration #158351

Enriched Foam Alcohol Hand Sanitizer

Newell Brands
1.800.347.9800

1000 mL (33.8 FL. OZ. U.S.)

© 2018 | 2080802 | 2082010 | 2081075 | V-08-2018
Made in the Netherlands